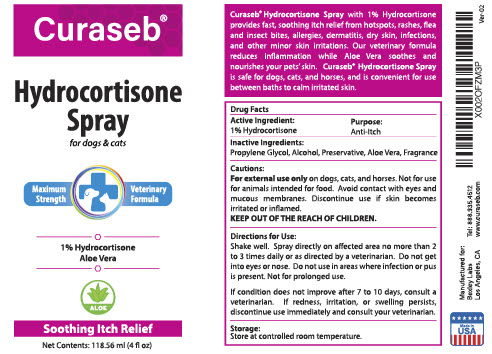 DRUG LABEL: Curaseb
NDC: 86133-002 | Form: SPRAY
Manufacturer: Bexley Labs
Category: animal | Type: OTC ANIMAL DRUG LABEL
Date: 20211228

ACTIVE INGREDIENTS: HYDROCORTISONE ACETATE 1 g/100 g
INACTIVE INGREDIENTS: PROPYLENE GLYCOL; ALCOHOL; ALOE VERA LEAF; DIAZOLIDINYL UREA

Curaseb® Hydrocortisone Spray

DESCRIPTION

Curaseb® Hydrocortisone Spray with 1% Hydrocortisone provides fast, soothing itch relief from hotspots, rashes, flea and insect bites, allergies, dermititis, dry skin, infections, and other minor skin irritations. Our non-stinging formula reduces inflammation while Aloe Vera soothes and nourishes your pets' skin. Curaseb® Hydrocortisone Spray is safe for dogs, cats, and horses, and is convenient for use between baths to calm irritated skin.

Active Ingredient: 1% Hydrocortisone

Purpose: Anti-Itch

Inactive INgredients:

Propylene Glycol, Alcohol, Preservative, Aloe, Fragrance

WARNINGS AND PRECAUTIONS

Cautions:

For External Use Only on dogs, cats, and horses. Not for use for animals intended for food. Avoid contact with eyes and mucous membranes. Discontinue use if the skin becomes irritated or inflamed.

KEEP OUT OF THE REACH OF CHILDREN.

Storage:

Store at controlled room temerature.

Made in USA

Manufactured for: Bexley Labs Los Angeles, CA

Tel: 888.935.4512

www.curaseb.com

X002OFZM3P

VER-02

PACKAGE LABEL

Curaseb® Hydrocortisone Spray for dogs & cats

Maximum Strength Veterinarian Formula

1% Hydrocortisone

Aloe Vera

Soothing Itch Relief

Net Contents: 118.56 (4 fl oz)